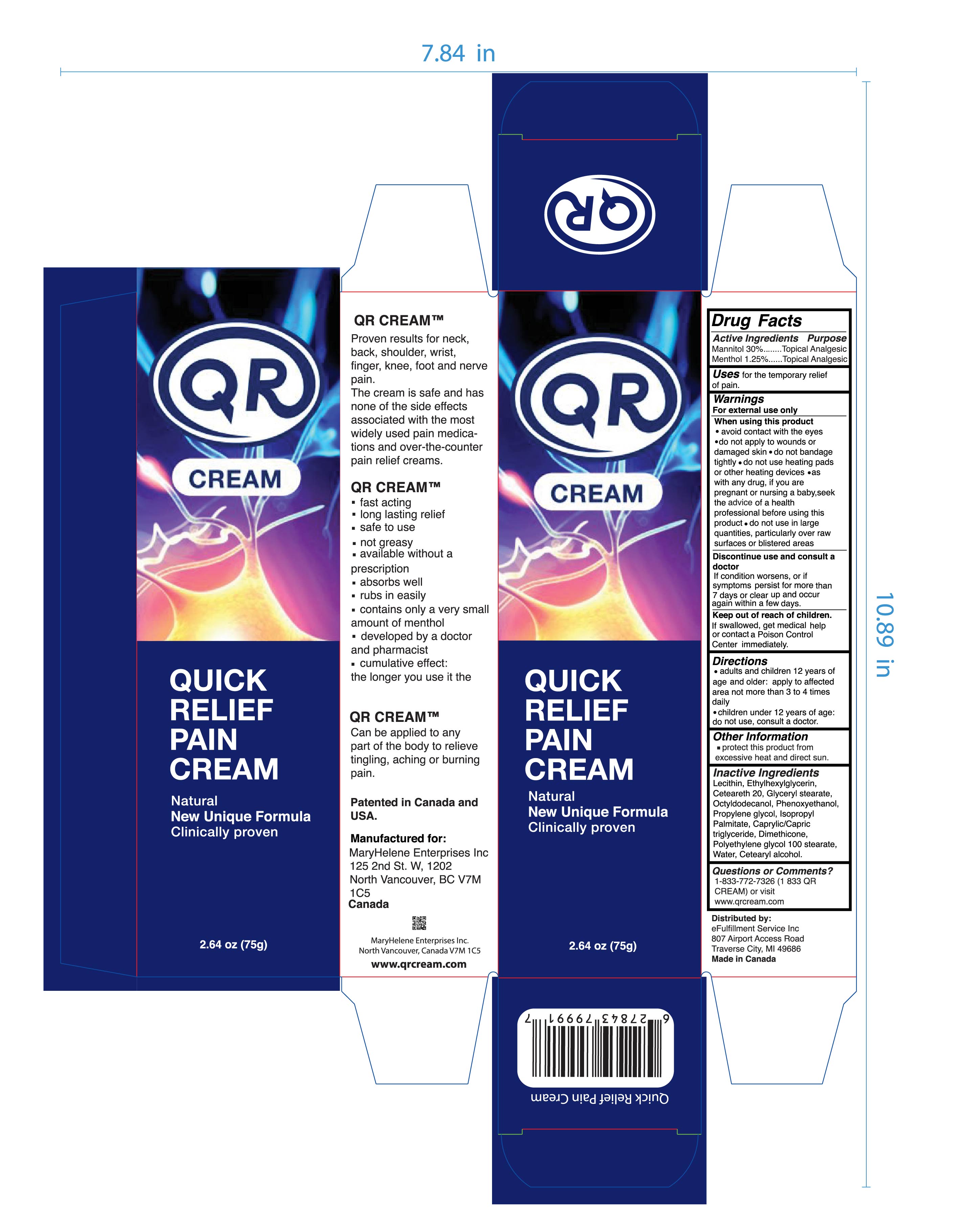 DRUG LABEL: QR PAIN
NDC: 73180-075 | Form: CREAM
Manufacturer: MARYHELENE ENTERPRISES INC
Category: otc | Type: HUMAN OTC DRUG LABEL
Date: 20251114

ACTIVE INGREDIENTS: MANNITOL 30 g/100 g; MENTHOL 1.25 g/100 g
INACTIVE INGREDIENTS: LECITHIN, SOYBEAN; ETHYLHEXYLGLYCERIN; POLYOXYL 20 CETOSTEARYL ETHER; GLYCERYL MONOSTEARATE; OCTYLDODECANOL; PHENOXYETHANOL; PROPYLENE GLYCOL; ISOPROPYL PALMITATE; MEDIUM-CHAIN TRIGLYCERIDES; DIMETHICONE; PEG-100 STEARATE; WATER; CETOSTEARYL ALCOHOL

QR PAIN CREAM 75g

Active Ingredient

Mannitol 30%

Menthol 1.25%

Purpose

Topical Analgesic

Uses

for the temporary relief of pain.

Warnings

For external use only.

When using this product

- do not bandage tightly
- avoid contact with the eyes
- do not apply to wounds or damaged skin
- do not use with heating pads or other heating devices
- as with any drug, if you are pregnant or nursing a baby, seek the advice of a health professional before using this product
- do not use in large quantities, particularly over raw surfaces or blistered areas.

Stop use and ask a doctor if

Condition worsens or if symptoms persist for more than 7 days or clear up and occur again within a few days.

Keep out of reach of children

If swallowed, get medical help or contact a Poison Control Center right away.

Directions

Adults and children 12 years of age and older, apply to affected area no more than 3-4 times a day. Children under 12 years of age: do not use, contact a doctor.

Other Information

Protect this product from excessive heat and direct sun.

Inactive Ingredients

Lecithin, Ethylhexylglycerin, Ceteareth 20, Glyceryl stearate, Octyldodecanol, Phenoxyethanol, Propylene glycol, Isopropyl Palmitate, Caprylic/Capric triglyceride, Dimethicone, Polyethylene glycol 100 stearate, Water, Cetearyl alcohol.

Questions or Comments?

1-833-772-7326 (1 833 QR CREAM) or visit www.qrcream.com